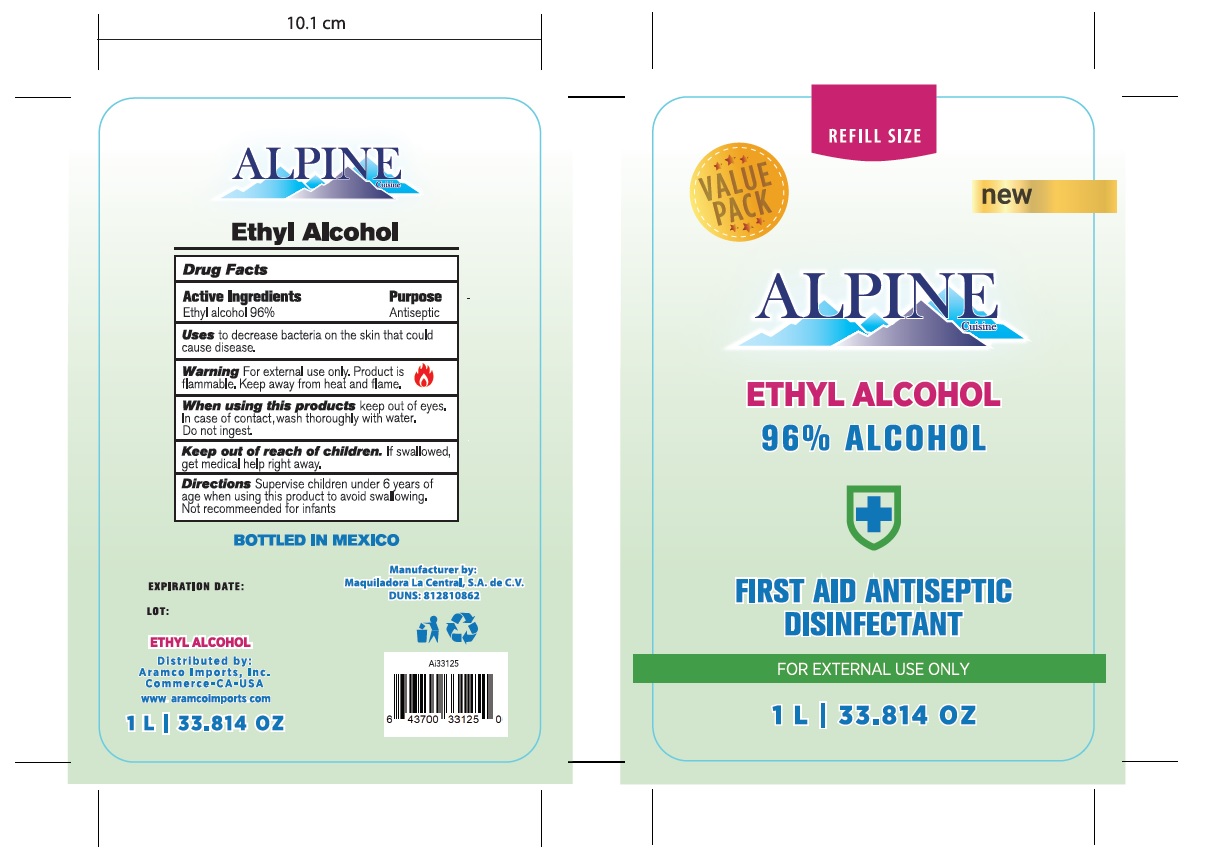 DRUG LABEL: ANTISEPTIC DISINFECTANT
NDC: 77217-200 | Form: LIQUID
Manufacturer: Maquiladora La Central, S.A. de C.V.
Category: otc | Type: HUMAN OTC DRUG LABEL
Date: 20200705

ACTIVE INGREDIENTS: ALCOHOL 96 mL/100 mL
INACTIVE INGREDIENTS: GLYCERIN; HYDROGEN PEROXIDE; WATER

The antiseptic disinfectant is manufactured using only the following United States Pharmacopoeia (USP) grade ingredients in the preparation of the product (percentage in final product formulation) consistent with World Health Organization (WHO) recommendations:

Ethyl Alcohol (ethanol) (USP or Food Chemical Codex (FCC) grade) (96%, volume/volume (v/v)) in an aqueous solution denatured according to Alcohol and Tobacco Tax and Trade Bureau regulations in 27 CFR part 20.

The firm does not add other active or inactive ingredients. Different or additional ingredients may impact the quality and potency of the product.

Active Ingredient(s)

Ethyl Alcohol 96% v/v. Purpose: Antiseptic

Purpose

Antiseptic

Use

Antiseptic Disinfectant to help reduce bacteria that potentially can cause disease.

Warnings

For external use only. Flammable. Keep away from heat or flame

Do not use

in children less than 2 months of age

When using this product keep out of eyes, ears, and mouth. In case of contact with eyes, rinse eyes thoroughly with water.
Stop use and ask a doctor if irritation or rash occurs. These may be signs of a serious condition.
Keep out of reach of children. If swallowed, get medical help or contact a Poison Control Center right away.

Stop use and ask a doctor if irritation or rash occurs. These may be signs of a serious condition.

Keep out of reach of children. If swallowed, get medical help or contact a Poison Control Center right away.

Directions

Place enough product to clean the infected area
Supervise children under 6 years of age when using this product to avoid swallowing.

Other information

Store between 15-30C (59-86F)
Avoid freezing and excessive heat above 40C (104F)

Inactive ingredients

purified water USP

Maximum 1000000000 mL in 1 CONTAINER (77217-200-05)

1000 mL NDC: 77217-200-05